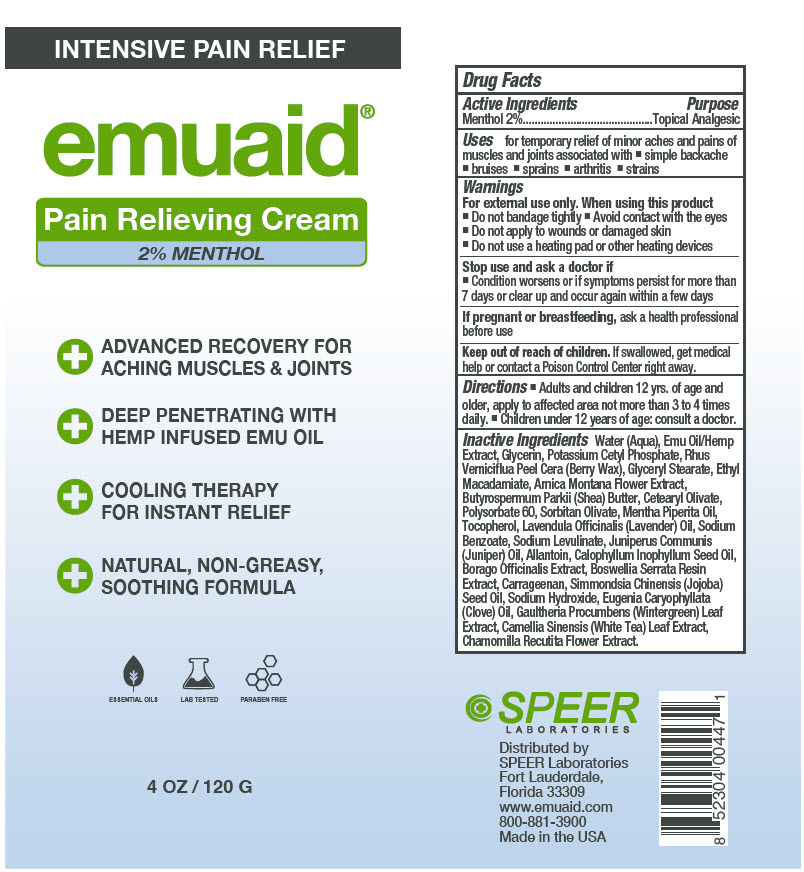 DRUG LABEL: EMUAID Pain Relieving
NDC: 55926-0026 | Form: CREAM
Manufacturer: Speer Laboratories LLC
Category: otc | Type: HUMAN OTC DRUG LABEL
Date: 20230623

ACTIVE INGREDIENTS: Menthol, Unspecified Form 2.4 g/120 g
INACTIVE INGREDIENTS: Water; Emu Oil; CANNABIS SATIVA FLOWERING TOP; Glycerin; Potassium Cetyl Phosphate; TOXICODENDRON VERNICIFLUUM FRUIT RIND WAX; Glyceryl Monostearate; Ethyl Macadamiate; Arnica Montana Flower; SHEA BUTTER; Cetearyl Olivate; Polysorbate 60; Sorbitan Olivate; Peppermint Oil; Tocopherol; LAVENDER OIL; Sodium Benzoate; Sodium Levulinate; JUNIPER BERRY OIL; Allantoin; Tamanu Oil; BORAGE; INDIAN FRANKINCENSE; Carrageenan; Jojoba Oil; Sodium Hydroxide; CLOVE OIL; Gaultheria Procumbens Leaf; GREEN TEA LEAF; CHAMOMILE

EMUAID® Pain Relieving Cream

Drug Facts

Active Ingredients

Menthol 2%

Purpose

Topical Analgesic

Uses

for temporary relief of minor aches and pains of muscles and joints associated with

- simple backache
- bruises
- sprains
- arthritis
- strains

Warnings

For external use only. When using this product

- Do not bandage tightly
- Avoid contact with the eyes
- Do not apply to wounds or damaged skin
- Do not use a heating pad or other heating devices

Stop use and ask a doctor if

- Condition worsens or if symptoms persist for more than 7 days or clear up and occur again within a few days

PREGNANCY OR BREAST FEEDING

If pregnant or breastfeeding, ask a health professional before use

Keep out of reach of children. If swallowed, get medical help or contact a Poison Control Center right away.

Directions

- Adults and children 12 yrs. of age and older, apply to affected area not more than 3 to 4 times daily.
- Children under 12 years of age: consult a doctor.

Inactive Ingredients

Water (Aqua), Emu Oil/Hemp Extract, Glycerin, Potassium Cetyl Phosphate, Rhus Verniciflua Peel Cera (Berry Wax), Glyceryl Stearate, Ethyl Macadamiate, Arnica Montana Flower Extract, Butyrospermum Parkii (Shea) Butter, Cetearyl Olivate, Polysorbate 60, Sorbitan Olivate, Mentha Piperita Oil, Tocopherol, Lavendula Officinalis (Lavender) Oil, Sodium Benzoate, Sodium Levulinate, Juniperus Communis (Juniper) Oil, Allantoin, Calophyllum Inophyllum Seed Oil, Borago Officinalis Extract, Boswellia Serrata Resin Extract, Carrageenan, Simmondsia Chinensis (Jojoba) Seed Oil, Sodium Hydroxide, Eugenia Caryophyllata (Clove) Oil, Gaultheria Procumbens (Wintergreen) Leaf Extract, Camellia Sinensis (White Tea) Leaf Extract, Chamomilla Recutita Flower Extract.

Distributed by
SPEER Laboratories
Fort Lauderdale,
Florida 33309

PRINCIPAL DISPLAY PANEL - 120 G Tube Label

INTENSIVE PAIN RELIEF

emuaid®

Pain Relieving Cream
2% MENTHOL

⊕ ADVANCED RECOVERY FOR
  ACHING MUSCLES & JOINTS
⊕ DEEP PENETRATING WITH
  HEMP INFUSED EMU OIL
⊕ COOLING THERAPY
  FOR INSTANT RELIEF
⊕ NATURAL, NON-GREASY,
  SOOTHING FORMULA

ESSENTIAL OILS
LAB TESTED
PARABEN FREE

4 OZ / 120 G